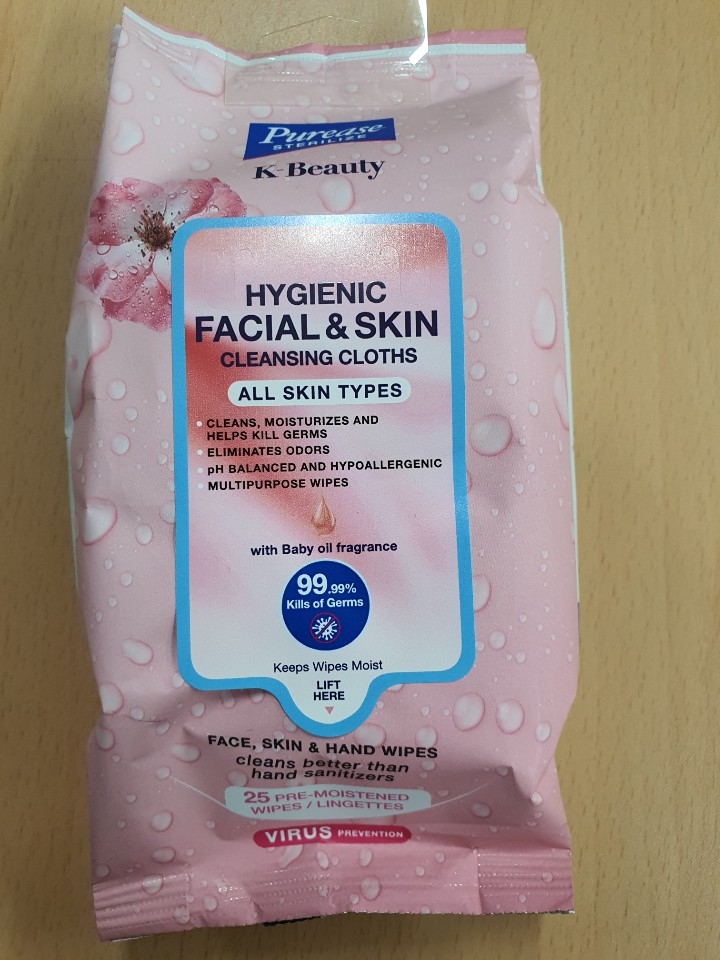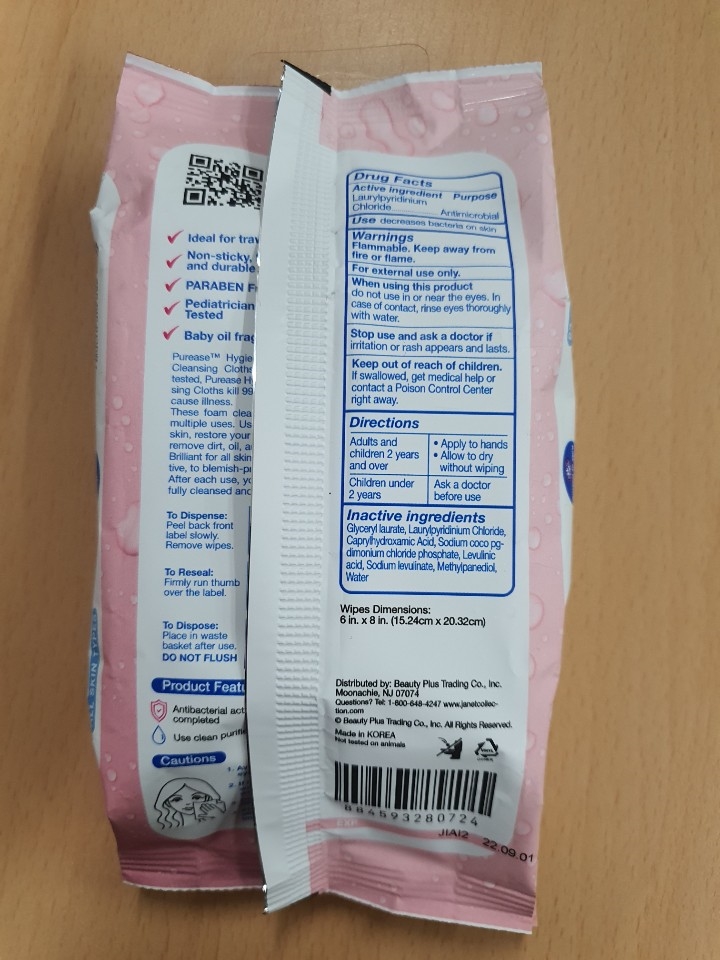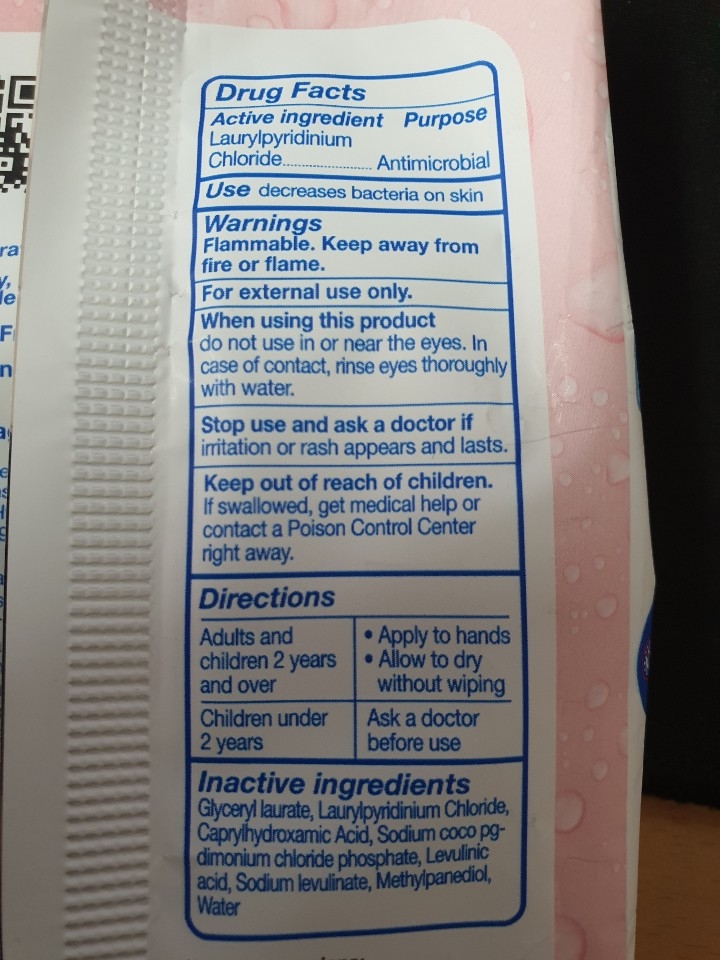 DRUG LABEL: Purease Hygienic Facial Skin Cleansing Cloths
NDC: 80503-201 | Form: LIQUID
Manufacturer: Eunhye Tissue
Category: otc | Type: HUMAN OTC DRUG LABEL
Date: 20200907

ACTIVE INGREDIENTS: LAURYLPYRIDINIUM CHLORIDE 0.07 g/100 g
INACTIVE INGREDIENTS: GLYCERYL LAURATE; CAPRYLHYDROXAMIC ACID; CHLORIDE ION; SODIUM LEVULINATE; LEVULINIC ACID; WATER; METHYLPROPANEDIOL

80503-201

Active ingredient

Laurylpyridinium Chloride 0.07%

Purpose

Antimicrobial

Use

decreases bacteria on skin

Warnings

Flammable. Keep away from fire or flame.

For external use only.

When using this product

do not use in or near the eyes. In case of contact, rinse eyes thoroughly with water.

Stop use and ask a doctor if

irritation or rash appears and lasts.

Keep out of reach of children.

If swallowed, get medical help or contact a Poison Control Center right away.

Directions

Adults and children 2 years and over

- Apply to hands
- Allow to dry without wiping

Children under 2 years

Ask a doctor before use

Inactive ingredients

Glyceryl laurate, Caprylhydroxamic Acid, Sodium coco pg-dimonium chloride phosphate, Levulinic acid, Sodium levulinate, Methylpanediol, Water